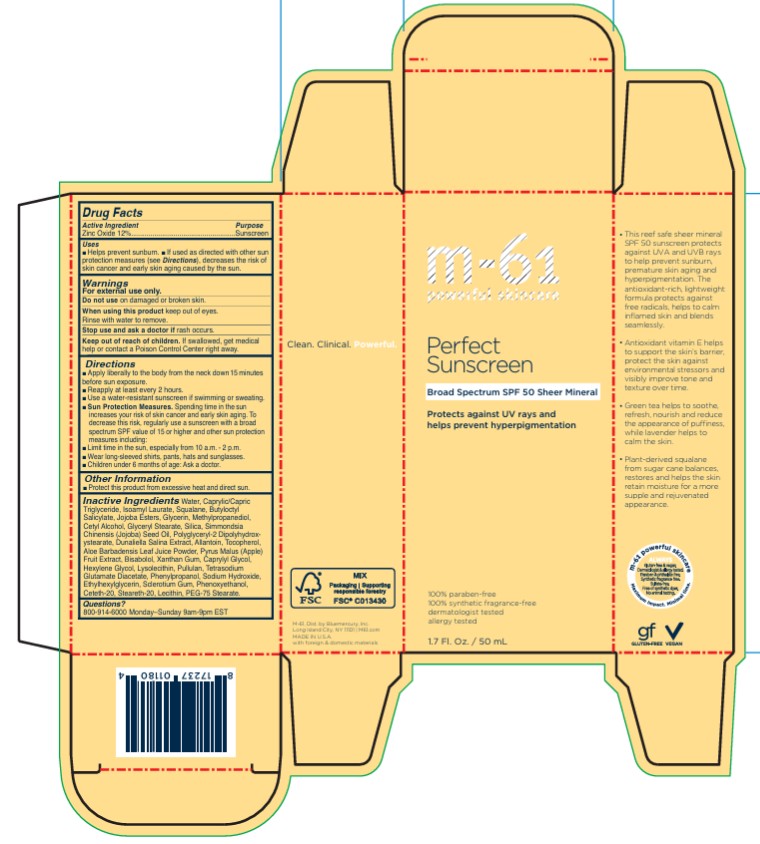 DRUG LABEL: Perfect Sunscreen SPF 50 Sheer Mineral
NDC: 72203-016 | Form: LOTION
Manufacturer: Bluemercury, Inc.
Category: otc | Type: HUMAN OTC DRUG LABEL
Date: 20251209

ACTIVE INGREDIENTS: ZINC OXIDE 0.12 g/1 mL
INACTIVE INGREDIENTS: LAVANDULA ANGUSTIFOLIA SUBSP. ANGUSTIFOLIA FLOWERING TOP; LAVANDULA ANGUSTIFOLIA SUBSP. ANGUSTIFOLIA FLOWER; SUNFLOWER OIL; APPLE; ALLANTOIN; LEVOMENOL; RUTIN; CAPRYLYL GLYCOL; BETASIZOFIRAN; FERRIC OXIDE RED; PHENYLPROPANOL; PULLULAN; XANTHAN GUM; ALKYL (C12-15) BENZOATE; POLYGLYCERYL-4 DIISOSTEARATE/POLYHYDROXYSTEARATE/SEBACATE; POLYGLYCERYL-2 DIPOLYHYDROXYSTEARATE; CETETH-20; STEARETH-20; TETRASODIUM GLUTAMATE DIACETATE; PHENOXYETHANOL; PEG-75 STEARATE; ETHYLHEXYLGLYCERIN; HEXYLENE GLYCOL; SODIUM HYDROXIDE; WATER; MEDIUM-CHAIN TRIGLYCERIDES; SQUALANE; ISOAMYL LAURATE; BUTYLOCTYL SALICYLATE; GLYCERIN; METHYLPROPANEDIOL; CETYL ALCOHOL; GLYCERYL MONOSTEARATE; SILICON DIOXIDE; TOCOPHEROL; .ALPHA.-TOCOPHEROL ACETATE; GREEN TEA LEAF

Perfect Sunscreen SPF 50 Tinted Mineral

Drug Facts

Active Ingredient

Zinc Oxide 12%

Purpose

sunscreen

Uses

- Helps prevent sunburn.
- If used as directed with other sun protection measures (see Directions), decreases the risk of skin cancer and early skin aging caused by the sun.

Warnings

For external use only.

Do not use on damaged or broken skin.

When using this product keep out of eyes. Rinse with water to remove.

Stop use and ask a doctor if rash occurs.

Keep out of reach of children.

If swallowed, get medical help or contact a Poison Control Center right away.

Directions

- Apply liberally 15 minutes before sun exposure.
- Reapply at least every 2 hours.
- Use a water resistant sunscreen if swimming or sweating.
- Sun Protection Measures. Spending time in the sun increases your risk of skin cancer and early skin aging. To decrease this risk, regularly use a sunscreen with a broad spectrum SPF of 15 or higher and other sun protection measures including:
  - Limit time in the sun, especially from 10am-2pm.
  - Wear long-sleeve shirts, pants, hats & sunglasses.
- Children under 6 months of age: Ask a doctor.

Inactive Ingredients

Water, Caprylic/Capric Triglyceride, Squalane, Isoamyl Laurate, Butyloctyl Salicylate, Glycerin, Jojoba Esters, Methylpropanediol, Cetyl Alcohol, Glyceryl Stearate, Silica, Tocopherol, Tocopheryl Acetate, Camellia Sinensis Leaf Extract, Lavandula Angustifolia (Lavender) Flower/Leaf/Stem Extract, Lavandula Angustifolia (Lavender) Flower Extract, Helianthus Annuus (Sunflower) Seed Oil, Pyrus Malus (Apple) Fruit Extract, Allantoin, Bisabolol, Rutin, Lecithin, Hydrogenated Lecithin, Lysolecithin, Caprylyl Glycol, Sclerotium Gum, Iron Oxides, Phenylpropanol, Pullulan, Xanthan Gum, C12-15 Alkyl Benzoate, Polyglyceryl-4 Diisostearate/Polyhydroxystearat e/Sebacate, Polyglyceryl-2 Dipolyhydroxystearate, Ceteth-20, Steareth-20, Tetrasodium Glutamate Diacetate, Phenoxyethanol, PEG-75 Stearate, Ethylhexylglycerin, Hexylene Glycol, Sodium Hydroxide

Other Information

- Protect the product in this container from excessive heat and direct sun.

Questions?

800-294-7700 9-5pm EST, Monday-Friday

PRINCIPAL DISPLAY PANEL - 50 mL Bottle Carton

m-61®
powerful skincare

Perfect
Sunscreen
SPF 50

Tinted Mineral

BROAD SPECTRUM SPF 50
VITAMIN E AND GREEN TEA
TINTED REEF SAFE MINERAL
SUNSCREEN

Tinted mineral SPF 50 with
vitamin E, green tea, lavender
and plant-derived squalane

all skin types

100% paraben-free
100% synthetic fragrance-free
dermatologist tested
allergy tested

50 mL/ 1.7 FL. OZ.